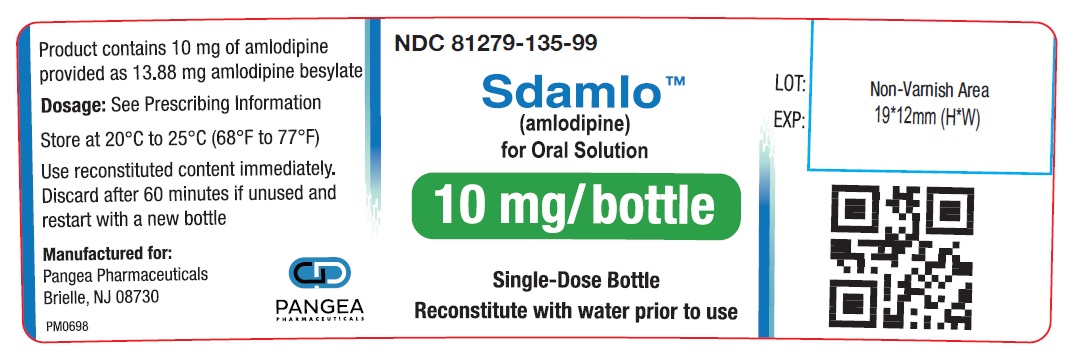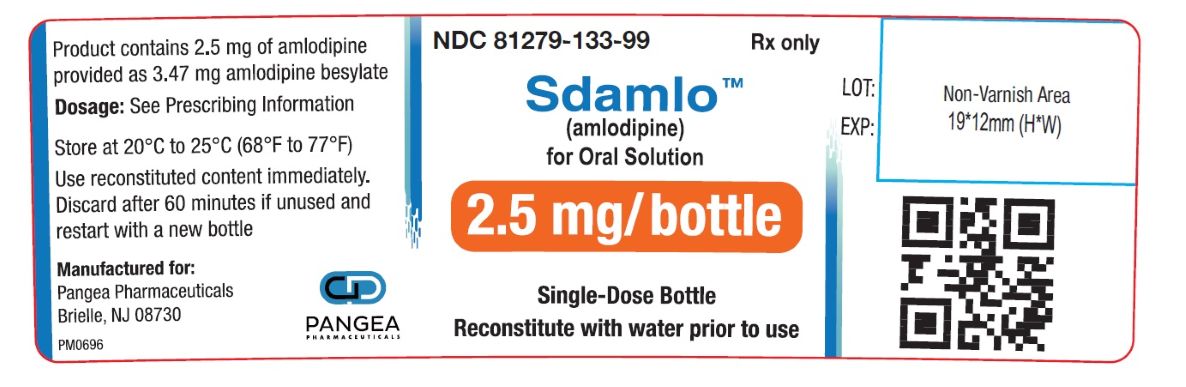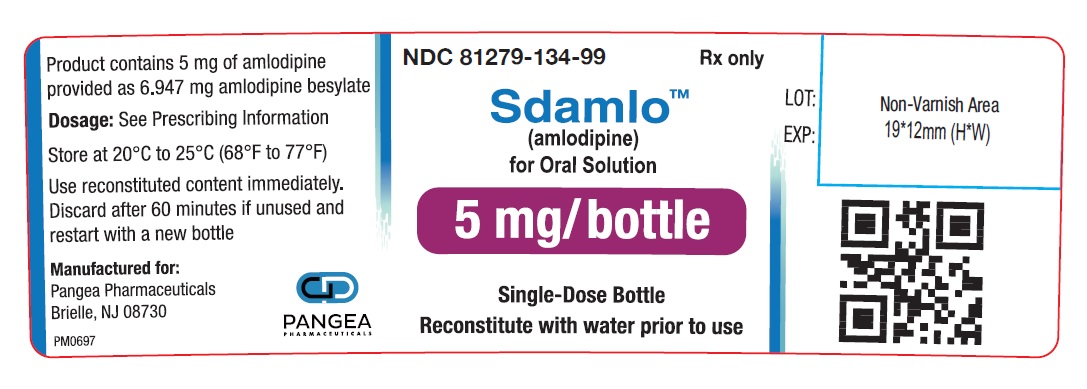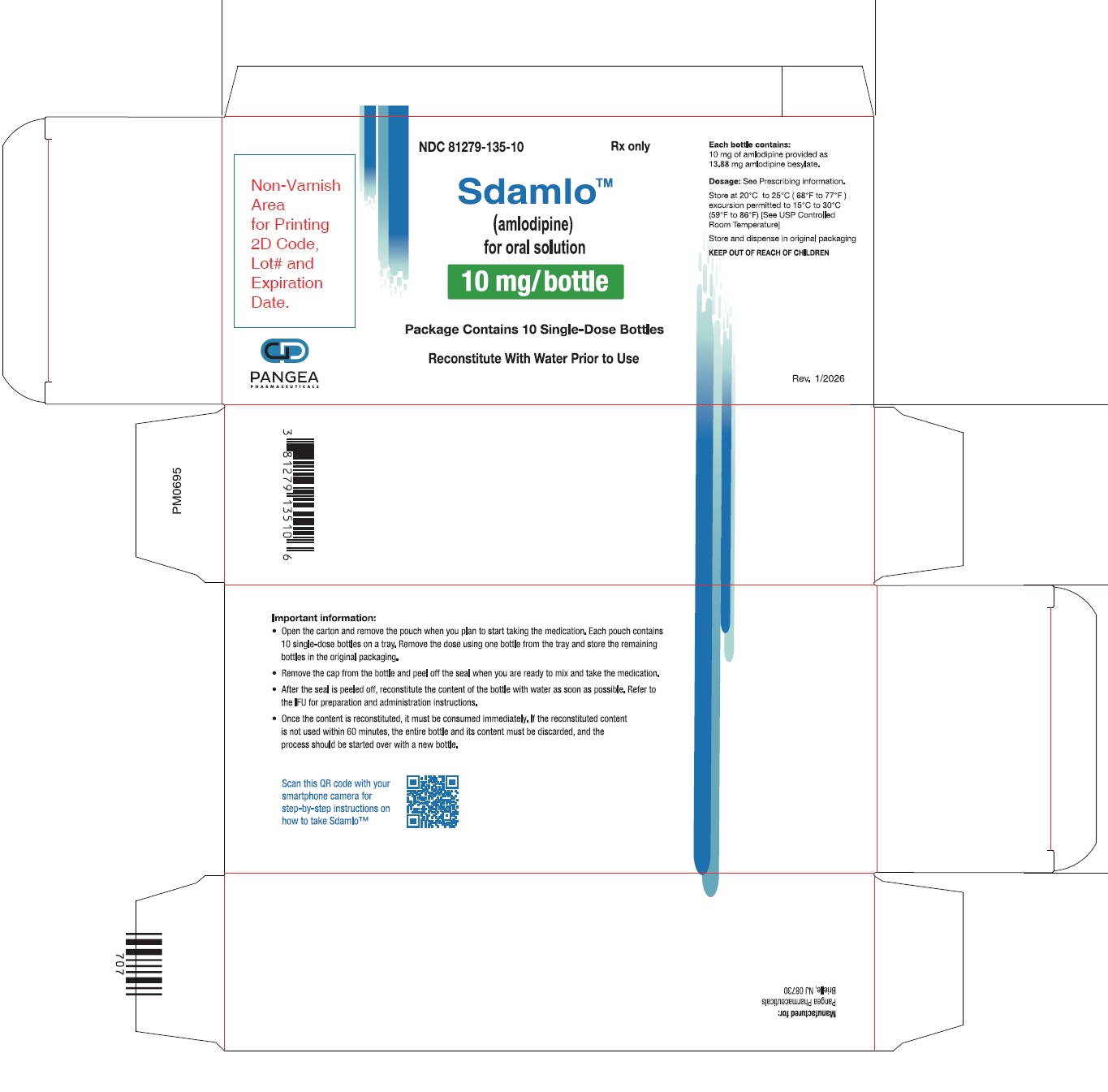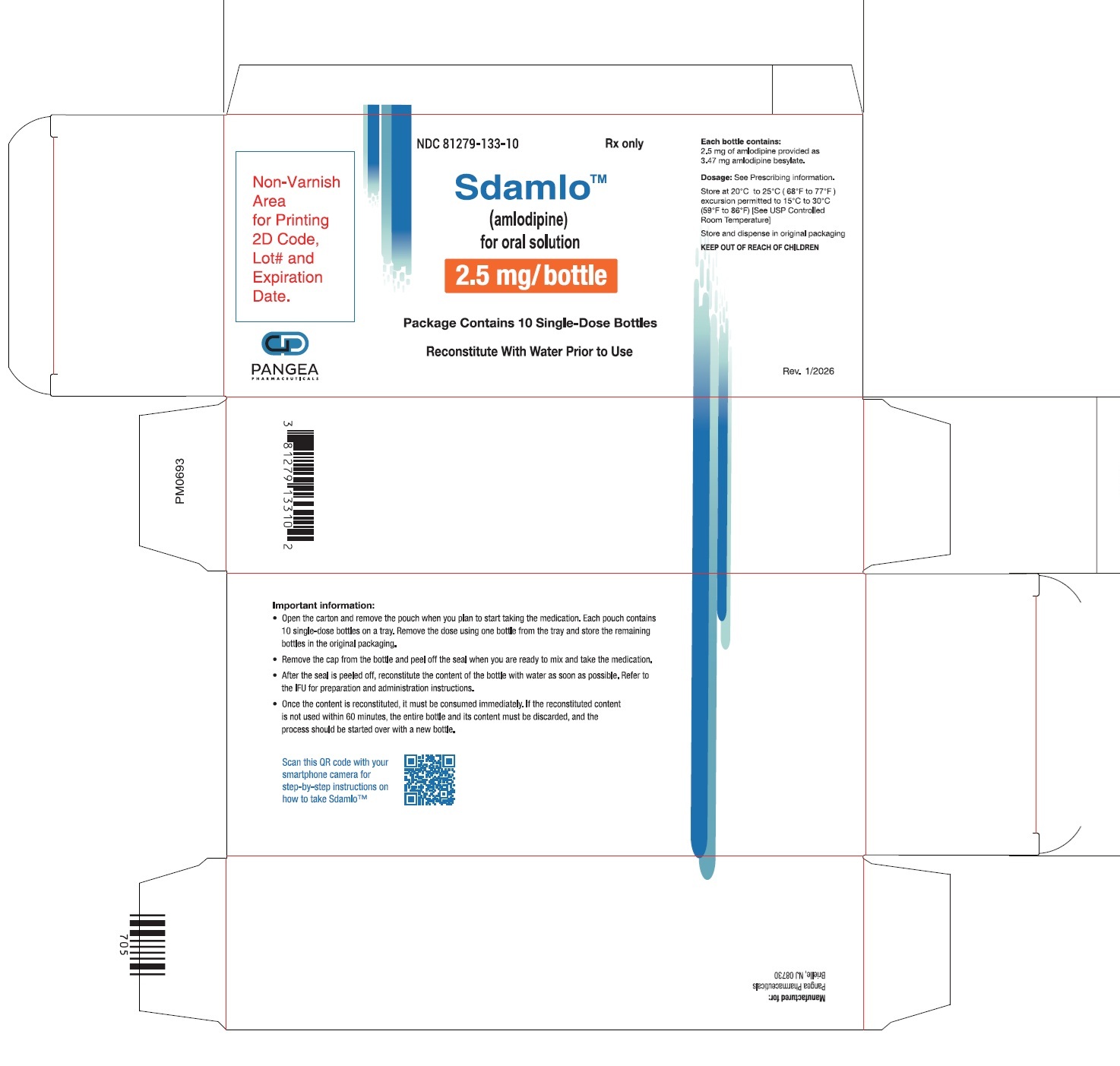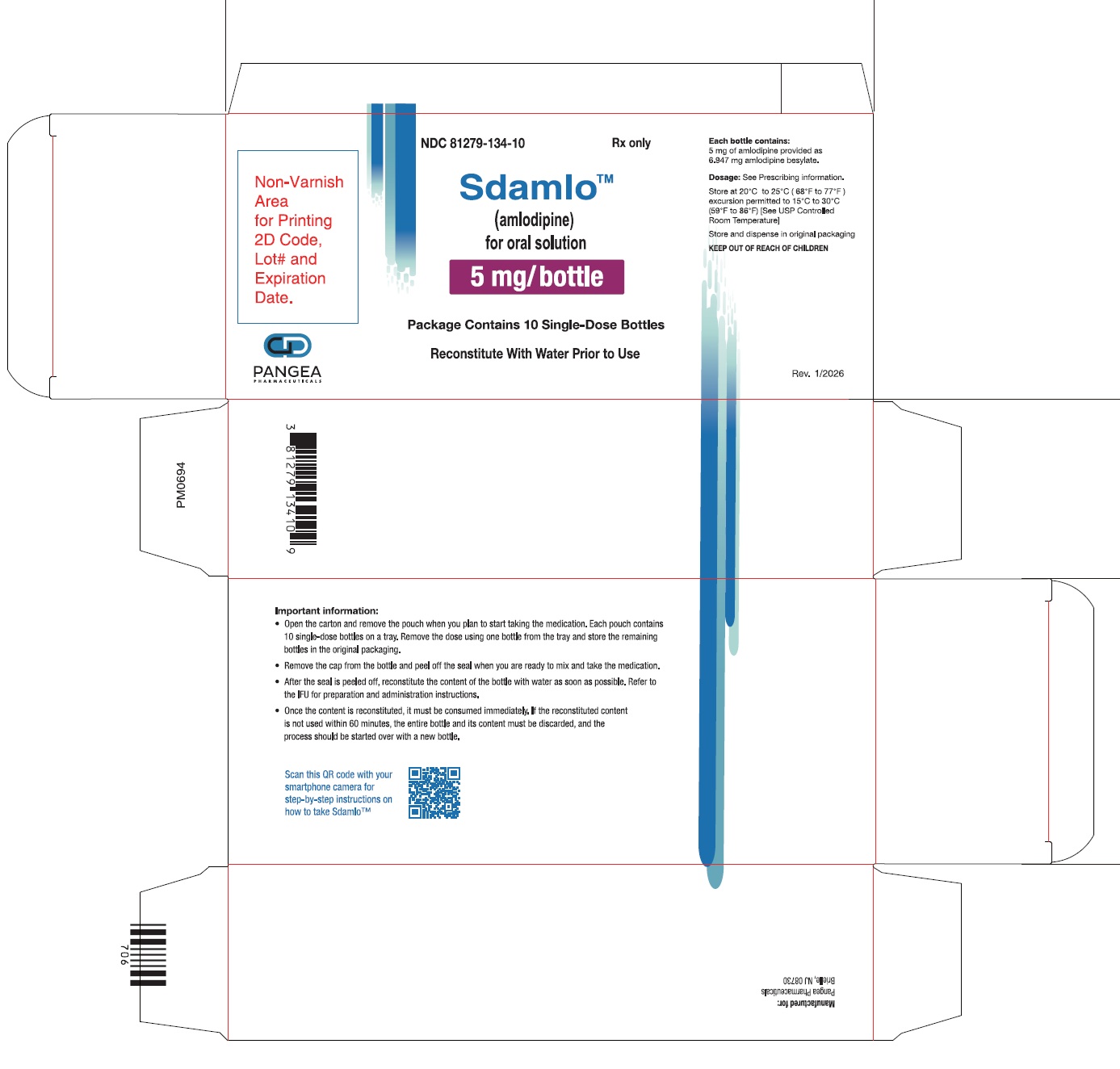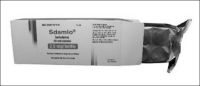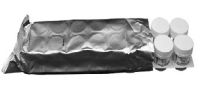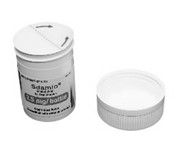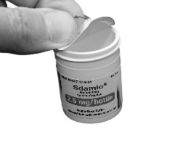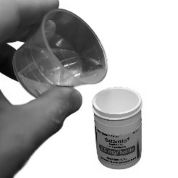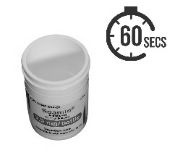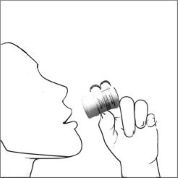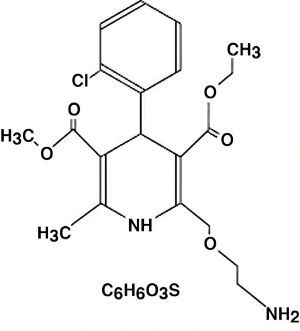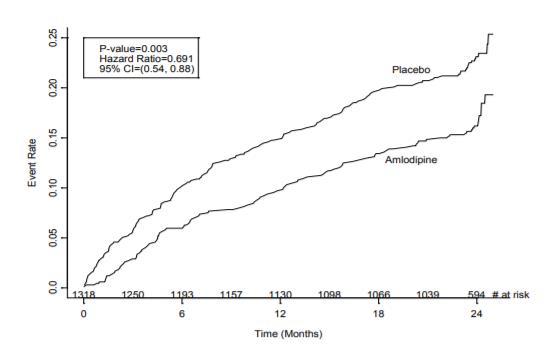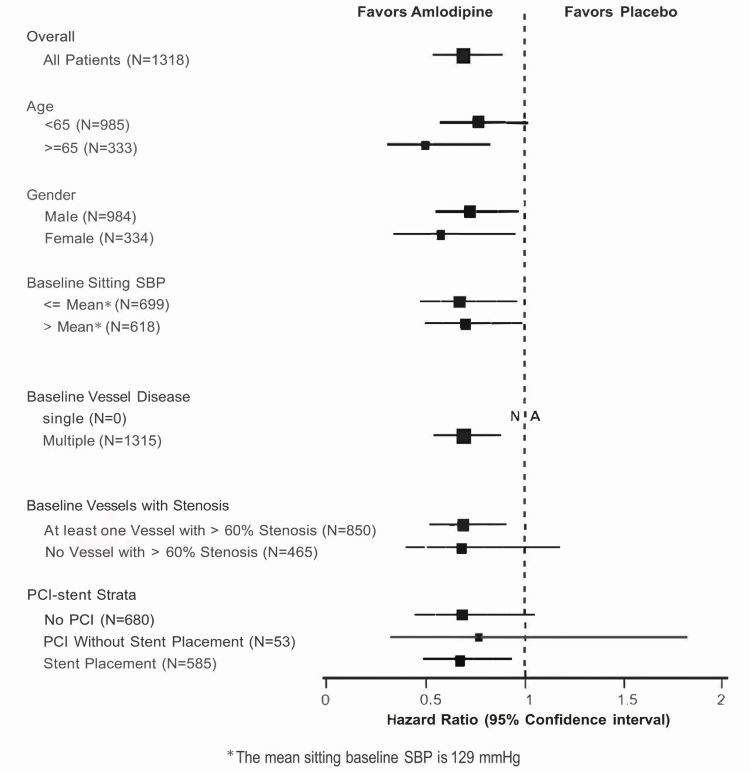 DRUG LABEL: Sdamlo
NDC: 81279-133 | Form: SOLUTION
Manufacturer: Pangea Pharmaceuticals, LLC
Category: prescription | Type: HUMAN PRESCRIPTION DRUG LABEL
Date: 20251103

ACTIVE INGREDIENTS: AMLODIPINE BESYLATE 2.5 mg/2.5 mg
INACTIVE INGREDIENTS: MANNITOL; NEOTAME

HIGHLIGHTS OF PRESCRIBING INFORMATION

These highlights do not include all the information needed to use Sdamlo safely and effectively. See full prescribing information for Sdamlo.
Sdamlo (amlodipine) for oral solution.
Initial U.S. Approval: 1992

1 INDICATIONS AND USAGE

Sdamlo is a calcium channel blocker and may be used alone or in combination with other antihypertensive and antianginal agents for the treatment of:

- Hypertension (1.1)
  - Sdamlo is indicated for the treatment of hypertension, to lower blood pressure in adults and pediatric patients 6 years of age and older. Lowering blood pressure reduces the risk of fatal and nonfatal cardiovascular events, primarily strokes and myocardial infarctions.
- Coronary Artery Disease in adults (1.2)
  - Chronic Stable Angina
  - Vasospastic Angina (Prinzmetal's or Variant Angina)
  - Angiographically Documented Coronary Artery Disease in patients without heart failure or an ejection fraction <40%

2 DOSAGE AND ADMINISTRATION

- Adult recommended starting dose: 5 mg orally once daily with maximum dose 10 mg orally once daily. (2.1)
  - Small, fragile, or elderly patients, or patients with hepatic insufficiency may be started on 2.5 mg orally once daily. (2.1)
- Pediatric starting dose: 2.5 mg to 5 mg orally once daily. (2.2)

Important Limitation: Doses in excess of 5 mg daily have not been studied in pediatric patients. (2.2)

3 DOSAGE FORMS AND STRENGTHS

For oral solution: 2.5 mg, 5 mg, and 10 mg (3)

4 CONTRAINDICATIONS

- Known sensitivity to amlodipine (4)

5 WARNINGS AND PRECAUTIONS

- Symptomatic hypotension is possible, particularly in patients with severe aortic stenosis. However, acute hypotension is unlikely. (5.1)
- Worsening angina and acute myocardial infarction can develop after starting or increasing the dose of Sdamlo, particularly in patients with severe obstructive coronary artery disease. (5.2)
- Titrate slowly in patients with severe hepatic impairment. (5.3)

6 ADVERSE REACTIONS

Most common adverse reaction to amlodipine is edema which occurred in a dose related manner. Other adverse experiences not dose related but reported with an incidence >1.0% are fatigue, nausea, abdominal pain, and somnolence. (6)

To report SUSPECTED ADVERSE REACTIONS, contact Pangea Pharmaceuticals at 1-855-892-8224 or FDA at 1-800-332-1088 or www.fda.gov/medwatch .

7 DRUG INTERACTIONS

- Do not exceed doses greater than 20 mg daily of simvastatin. (7.2)

8 USE IN SPECIFIC POPULATIONS

- Pediatric: Effect on patients less than 6 years old is not known. (8.4)
- Geriatric: Start dosing at the low end of the dose range. (8.5)

See 17 for PATIENT COUNSELING INFORMATION.

FULL PRESCRIBING INFORMATION

1 INDICATIONS AND USAGE

1.1 Hypertension

Sdamlo is indicated for the treatment of hypertension, to lower blood pressure in adults and pediatric patients 6 years of age and older. Lowering blood pressure reduces the risk of fatal and nonfatal cardiovascular events, primarily strokes and myocardial infarctions. These benefits have been seen in controlled trials of antihypertensive drugs from a wide variety of pharmacologic classes including amlodipine.

Control of high blood pressure should be part of comprehensive cardiovascular risk management, including, as appropriate, lipid control, diabetes management, antithrombotic therapy, smoking cessation, exercise, and limited sodium intake. Many patients will require more than one drug to achieve blood pressure goals. For specific advice on goals and management, see published guidelines, such as those of the National High Blood Pressure Education Program’s Joint National Committee on Prevention, Detection, Evaluation, and Treatment of High Blood Pressure (JNC).

Numerous antihypertensive drugs, from a variety of pharmacologic classes and with different mechanisms of action, have been shown in randomized controlled trials to reduce cardiovascular morbidity and mortality, and it can be concluded that it is blood pressure reduction, and not some other pharmacologic property of the drugs, that is largely responsible for those benefits. The largest and most consistent cardiovascular outcome benefit has been a reduction in the risk of stroke, but reductions in myocardial infarction and cardiovascular mortality also have been seen regularly.

Elevated systolic or diastolic pressure causes increased cardiovascular risk, and the absolute risk increase per mmHg is greater at higher blood pressures, so that even modest reductions of severe hypertension can provide substantial benefit. Relative risk reduction from blood pressure reduction is similar across populations with varying absolute risk, so the absolute benefit is greater in patients who are at higher risk independent of their hypertension (for example, patients with diabetes or hyperlipidemia), and such patients would be expected to benefit from more aggressive treatment to a lower blood pressure goal.

Some antihypertensive drugs have smaller blood pressure effects (as monotherapy) in black patients, and many antihypertensive drugs have additional approved indications and effects (e.g., on angina, heart failure, or diabetic kidney disease). These considerations may guide selection of therapy.

Sdamlo may be used alone or in combination with other antihypertensive agents.

1.2 Coronary Artery Disease (CAD)

Chronic Stable Angina
Sdamlo is indicated for the symptomatic treatment of chronic stable angina in adults. Sdamlo may be used alone or in combination with other antianginal agents.

Vasospastic-Angina (Prinzmetal's or Variant Angina)
Sdamlo is indicated for the treatment of confirmed or suspected vasospastic angina in adults. Sdamlo may be used as monotherapy or in combination with other antianginal agents.

Angiographically Documented CAD
In adult patients with recently documented CAD by angiography and without heart failure or an ejection fraction <40%, Sdamlo is indicated to reduce the risk of hospitalization for angina and to reduce the risk of a coronary revascularization procedure.

2 DOSAGE AND ADMINISTRATION

2.1 Recommended Dosage in Adults

Hypertension

The usual initial antihypertensive oral dose of Sdamlo is 5 mg orally once daily, and the maximum dose is 10 mg orally once daily.

Small, fragile, or elderly patients, or patients with hepatic insufficiency may be started on 2.5 mg orally once daily and this dose may be used when adding Sdamlo to other antihypertensive therapy.

Adjust dosage according to blood pressure goals. In general, wait 7 to 14 days between titration steps. Titrate more rapidly, however, if clinically warranted, provided the patient is assessed frequently.

Angina

The recommended dose for chronic stable or vasospastic angina is 5 mg to 10 mg orally once daily, with the lower dose suggested in the elderly and in patients with hepatic insufficiency. Most patients will require 10 mg orally once daily for adequate effect.

Coronary Artery Disease

The recommended dose range for patients with coronary artery disease is 5 mg to 10 mg once daily. In clinical studies, the majority of patients required 10 mg orally once daily [see Clinical Studies (14.4)] .

2.2 Recommended Dosage in Pediatric Patients for Hypertension

The recommended antihypertensive dose in pediatric patients ages 6 to 17 years is 2.5 mg to 5 mg orally once daily. Doses in excess of 5 mg orally once daily have not been studied in pediatric patients [see Clinical Pharmacology (12.4), Clinical Studies (14.1)] .

2.3 Preparation and Administration of Sdamlo for Oral Solution

• Remove the cap and peel off the seal.

• Use one tablespoon to measure 15 mL of room temperature water. Add the 15 ml water to the container.

• Wait for 60 seconds to allow the content to fully dissolve. Shaking the container is not required.

• Consume the entire content of the container immediately or within 60 minutes.

• Rinse the container with similar amount of water 1 to 2 times and consume the rinses.

3 DOSAGE FORMS AND STRENGTHS

Sdamlo for Oral Solution 2.5 mg: each unit-dose bottle contains 2.5 mg of amlodipine as a white to off-white dry powder or powder cake.

Sdamlo for Oral Solution 5 mg: each unit-dose bottle contains 5 mg of amlodipine as a white to off-white dry powder or powder cake.

Sdamlo for Oral Solution 10 mg: each unit-dose bottle contains 10 mg of amlodipine as a white to off-white dry powder or powder cake.

4 CONTRAINDICATIONS

Sdamlo is contraindicated in patients with known sensitivity to amlodipine.

5 WARNINGS AND PRECAUTIONS

5.1 Hypotension

Symptomatic hypotension is possible, particularly in patients with severe aortic stenosis. Because of the gradual onset of action, acute hypotension is unlikely.

5.2 Increased Angina or Myocardial Infarction

Worsening angina and acute myocardial infarction can develop after starting or increasing the dose of Sdamlo, particularly in patients with severe obstructive coronary artery disease.

5.3 Patients with Hepatic Failure

Because amlodipine is extensively metabolized by the liver and the plasma elimination half-life (t1/2) is 56 hours in patients with impaired hepatic function, titrate slowly when administering Sdamlo to patients with severe hepatic impairment.

6 ADVERSE REACTIONS

6.1 Clinical Trials Experience

Because clinical trials are conducted under widely varying conditions, adverse reaction rates observed in the clinical trials of a drug cannot be directly compared to rates in the clinical trials of another drug and may not reflect the rates observed in practice.

Amlodipine has been evaluated for safety in more than 11,000 patients in U.S. and foreign clinical trials. In general, treatment with amlodipine was well-tolerated at doses up to 10 mg daily. Most adverse reactions reported during therapy with amlodipine were of mild or moderate severity. In controlled clinical trials directly comparing amlodipine (N=1730) at doses up to 10 mg to placebo (N=1250), discontinuation of amlodipine because of adverse reactions was required in only about 1.5% of patients and was not significantly different from placebo (about 1%). The most commonly reported side effects more frequent than placebo are reflected in the table below. The incidence (%) of side effects that occurred in a dose related manner are as follows:

 | Amlodipine |  |  | Placebo
 | 2.5 mg N=275 | 5 mg N=296 | 10 mg N=268 | N=520
Edema | 1.8 | 3.0 | 10.8 | 0.6
Dizziness | 1.1 | 3.4 | 3.4 | 1.5
Flushing | 0.7 | 1.4 | 2.6 | 0.0
Palpitation | 0.7 | 1.4 | 4.5 | 0.6

Other adverse reactions that were not clearly dose related but were reported with an incidence greater than 1.0% in placebo-controlled clinical trials include the following:

 | Amlodipine (%) (N=1730) | Placebo (%) (N=1250)
Fatigue | 4.5 | 2.8
Nausea | 2.9 | 1.9
Abdominal Pain | 1.6 | 0.3
Somnolence | 1.4 | 0.6

For several adverse reactions, there was a greater incidence in women than men associated with amlodipine treatment as show in the following table:

 | Amlodipine |  | Placebo
 | Male=% (N=1218) | Female=% (N=512) | Male=% (N=914) | Female=% (N=336)
Edema | 5.6 | 14.6 | 1.4 | 5.1
Flushing | 1.5 | 4.5 | 0.3 | 0.9
Palpitations | 1.4 | 3.3 | 0.9 | 0.9
Somnolence | 1.3 | 1.6 | 0.8 | 0.3

The safety of amlodipine at doses of 2.5 mg and 5 mg once daily was evaluated in a randomized placebo-controlled trial in 268 pediatric patients aged 6 to 17 years with hypertension [see Clinical Studies (14.1)]. Adverse reactions were similar to those in adults.

6.2 Postmarketing Experience

The following adverse reactions have been identified during post-approval use of amlodipine. Because these reactions are reported voluntarily from a population of uncertain size, it is not always possible to reliably estimate their frequency or establish a causal relationship to drug exposure.

General: gynecomastia

Hepatic: jaundice and hepatic enzyme elevations, some require hospitalization.

Neurologic: extrapyramidal disorder.

7 DRUG INTERACTIONS

7.1 Impact of Other Drugs on Amlodipine

CYP3A Inhibitors
Co-administration with CYP3A inhibitors (moderate and strong) results in increased systemic exposure to amlodipine and may require dose reduction. Monitor for symptoms of hypotension and edema when amlodipine is co-administered with CYP3A inhibitors to determine the need for dose adjustment [see Clinical Pharmacology (12.3)] .

CYP3A Inducers
No information is available on the quantitative effects of CYP3A inducers on amlodipine. Blood pressure should be closely monitored when amlodipine is co-administered with CYP3A inducers.

Sildenafil

Monitor for hypotension when sildenafil is co-administered with amlodipine [see Clinical Pharmacology (12.2)].

7.2 Impact of Amlodipine on Other Drugs

Simvastatin
Co-administration of simvastatin with amlodipine increases the systemic exposure of simvastatin. Limit the dose of simvastatin in patients on amlodipine to 20 mg daily [see Clinical Pharmacology (12.3)] .

Immunosuppressants
Amlodipine may increase the systemic exposure of cyclosporine or tacrolimus when co-administered. Frequent monitoring of trough blood levels of cyclosporine and tacrolimus is recommended and adjust the dose when appropriate [see Clinical Pharmacology (12.3)] .

8 USE IN SPECIFIC POPULATIONS

8.1 Pregnancy

Risk Summary
The limited available data based on post-marketing reports with amlodipine use in pregnant women are not sufficient to inform a drug-associated risk for major birth defects and miscarriage. There are risks to the mother and fetus associated with poorly controlled hypertension in pregnancy [see Clinical Considerations]. In animal reproduction studies, there was no evidence of adverse developmental effects when pregnant rats and rabbits were treated orally with amlodipine maleate during organogenesis at doses approximately 10 and 20-times the maximum recommended human dose (MRHD), respectively. However, for rats, litter size was significantly decreased (by about 50%) and the number of intrauterine deaths was significantly increased (about 5-fold). Amlodipine has been shown to prolong both the gestation period and the duration of labor in rats at this dose [see Data].

The estimated background risk of major birth defects and miscarriage for the indicated population is unknown. All pregnancies have a background risk of birth defect, loss or other adverse outcomes. In the U.S. general population, the estimated background risk of major birth defects and miscarriage in clinically recognized pregnancies is 2%–4% and 15%–20%, respectively.

Clinical Considerations
Disease-associated maternal and/or embryo/fetal risk
Hypertension in pregnancy increases the maternal risk for pre-eclampsia, gestational diabetes, premature delivery, and delivery complications (e.g., need for cesarean section and post-partum hemorrhage).

Hypertension increases the fetal risk for intrauterine growth restriction and intrauterine death. Pregnant women with hypertension should be carefully monitored and managed accordingly.

Data
Animal Data
No evidence of teratogenicity or other embryo/fetal toxicity was found when pregnant rats and rabbits were treated orally with amlodipine maleate at doses up to 10 mg amlodipine/kg/day (approximately 10 and 20 times the MRHD based on body surface area, respectively) during their respective periods of major organogenesis. However, for rats, litter size was significantly decreased (by about 50%) and the number of intrauterine deaths was significantly increased (about 5-fold) in rats receiving amlodipine maleate at a dose equivalent to 10 mg amlodipine/kg/day for 14 days before mating and throughout mating and gestation. Amlodipine maleate has been shown to prolong both the gestation period and the duration of labor in rats at this dose.

8.2 Lactation

Risk Summary
Limited available data from a published clinical lactation study reports that amlodipine is present in human milk at an estimated median relativeinfant dose of 4.2%. No adverse effects of amlodipine on the breastfed infant have been observed. There is no available information on the effects of amlodipine on milk production.

8.4 Pediatric Use

The safety and effectiveness of amlodipine for the treatment of hypertension have been established in pediatric patients aged 6 to 17 years. Use of amlodipine in this age group is supported by evidence from a randomized, placebo-controlled trial in pediatric patients 6 to 17 years of age with hypertension. [see Adverse Reactions (6.1)and Clinical Studies (14.1)] .

The safety and effectiveness of amlodipine have not been established in pediatric patients less than 6 years of age.

8.5 Geriatric Use

Clinical studies of amlodipine did not include sufficient numbers of subjects aged 65 and over to determine whether they respond differently from younger subjects. Other reported clinical experience has not identified differences in responses between the elderly and younger patients. In general, dose selection for an elderly patient should be cautious, usually starting at the low end of the dosing range, reflecting the greater frequency of decreased hepatic, renal, or cardiac function, and of concomitant disease or other drug therapy. Elderly patients have decreased clearance of amlodipine with a resulting increase of AUC of approximately 40–60%, and a lower initial dose may be required [see Dosage and Administration (2.1)] .

8.6 Hepatic Impairment

A lower initial dose may be required for patients with hepatic insufficiency [see Dosage and Administration (2.1) and Clinical Pharmacology (12.3)] .

10 OVERDOSAGE

Overdosage might be expected to cause excessive peripheral vasodilation with marked hypotension and possibly a reflex tachycardia. In humans, experience with intentional overdosage of amlodipine is limited.

Single oral doses of amlodipine maleate equivalent to 40 mg amlodipine/kg and 100 mg amlodipine/kg in mice and rats, respectively, caused deaths. Single oral amlodipine maleate doses equivalent to 4 or more mg amlodipine/kg or higher in dogs (11 or more times the maximum recommended human dose on a mg/m^2basis) caused a marked peripheral vasodilation and hypotension.

If massive overdose should occur, initiate active cardiac and respiratory monitoring. Frequent blood pressure measurements are essential. Should hypotension occur, provide cardiovascular support including elevation of the extremities and the judicious administration of fluids. If hypotension remains unresponsive to these conservative measures, consider administration of vasopressors (such as phenylephrine) with attention to circulating volume and urine output. As amlodipine is highly protein bound, hemodialysis is not likely to be of benefit.

11 DESCRIPTION

Sdamlo contains the besylate salt of amlodipine, a long-acting calcium channel blocker.

Amlodipine besylate is chemically described as 3-Ethyl-5-methyl (±)-2-[(2-aminoethoxy)methyl]-4-(2-chlorophenyl)-1,4-dihydro-6-methyl-3,5 pyridinedicarboxylate, monobenzenesulphonate. Its empirical formula is C20H25CIN2O5•C6H6O3S, and its structural formula is:

Amlodipine besylate is a white crystalline powder with a molecular weight of 567.1. It is slightly soluble in water and sparingly soluble in ethanol.

Sdamlo is supplied as a white to off-white powder or powder cake packaged in a unit-dose, single-use container. Each vial of Sdamlo contains 2.5, 5, and 10 mg of amlodipine, provided as 3.47, 6.94, and 13.88 mg of amlodipine besylate, respectively, and the following inactive ingredients: mannitol and neotame.

Sdamlo is for oral administration after reconstitution with water [see Dosage and Administration (2.3)] .

12 CLINICAL PHARMACOLOGY

12.1 Mechanism of Action

Amlodipine is a dihydropyridine calcium antagonist (calcium ion antagonist or slow-channel blocker) that inhibits the transmembrane influx of calcium ions into vascular smooth muscle and cardiac muscle. Experimental data suggest that amlodipine binds to both dihydropyridine and nondihydropyridine binding sites. The contractile processes of cardiac muscle and vascular smooth muscle are dependent upon the movement of extracellular calcium ions into these cells through specific ion channels.

Amlodipine inhibits calcium ion influx across cell membranes selectively, with a greater effect on vascular smooth muscle cells than on cardiac muscle cells. Negative inotropic effects can be detected in vitro but such effects have not been seen in intact animals at therapeutic doses. Serum calcium concentration is not affected by amlodipine. Within the physiologic pH range, amlodipine is an ionized compound (pKa=8.6), and its kinetic interaction with the calcium channel receptor is characterized by a gradual rate of association and dissociation with the receptor binding site, resulting in a gradual onset of effect.

Amlodipine is a peripheral arterial vasodilator that acts directly on vascular smooth muscle to cause a reduction in peripheral vascular resistance and reduction in blood pressure.

The precise mechanisms by which amlodipine relieves angina have not been fully delineated, but are thought to include the following:

Exertional Angina: In patients with exertional angina, amlodipine reduces the total peripheral resistance (afterload) against which the heart works and reduces the rate pressure product, and thus myocardial oxygen demand, at any given level of exercise.

Vasospastic Angina: amlodipine has been demonstrated to block constriction and restore blood flow in coronary arteries and arterioles in response to calcium, potassium epinephrine, serotonin, and thromboxane A2 analog in experimental animal models and in human coronary vessels in vitro. This inhibition of coronary spasm is responsible for the effectiveness of amlodipine in vasospastic (Prinzmetal’s or variant) angina.

12.2 Pharmacodynamics

Hemodynamics: Following administration of therapeutic doses to patients with hypertension, amlodipine produces vasodilation resulting in a reduction of supine and standing blood pressures. These decreases in blood pressure are not accompanied by a significant change in heart rate or plasma catecholamine levels with chronic dosing. Although the acute intravenous administration of amlodipine decreases arterial blood pressure and increases heart rate in hemodynamic studies of patients with chronic stable angina, chronic oral administration of amlodipine in clinical trials did not lead to clinically significant changes in heart rate or blood pressures in normotensive patients with angina.

With chronic once daily oral administration, antihypertensive effectiveness is maintained for at least 24 hours. Plasma concentrations correlate with effect in both young and elderly patients. The magnitude of reduction in blood pressure with amlodipine is also correlated with the height of pretreatment elevation; thus, individuals with moderate hypertension (diastolic pressure 105–114 mmHg) had about a 50% greater response than patients with mild hypertension (diastolic pressure 90–104 mmHg). Normotensive subjects experienced no clinically significant change in blood pressures (+1/–2 mmHg).

In hypertensive patients with normal renal function, therapeutic doses of amlodipine resulted in a decrease in renal vascular resistance and an increase in glomerular filtration rate and effective renal plasma flow without change in filtration fraction or proteinuria.

As with other calcium channel blockers, hemodynamic measurements of cardiac function at rest and during exercise (or pacing) in patients with normal ventricular function treated with amlodipine have generally demonstrated a small increase in cardiac index without significant influence on dP/dt or on left ventricular end diastolic pressure or volume. In hemodynamic studies, amlodipine has not been associated with a negative inotropic effect when administered in the therapeutic dose range to intact animals and man, even when co-administered with beta-blockers to man. Similar findings, however, have been observed in normal or well-compensated patients with heart failure with agents possessing significant negative inotropic effects.

Electrophysiologic Effects: amlodipine does not change sinoatrial nodal function or atrioventricular conduction in intact animals or man. In patients with chronic stable angina, intravenous administration of 10 mg did not significantly alter A-H and H-V conduction and sinus node recovery time after pacing. Similar results were obtained in patients receiving amlodipine and concomitant beta-blockers. In clinical studies in which amlodipine was administered in combination with beta-blockers to patients with either hypertension or angina, no adverse effects on electrocardiographic parameters were observed. In clinical trials with angina patients alone, amlodipine therapy did not alter electrocardiographic intervals or produce higher degrees of AV blocks.

Drug Interactions

Sildenafil:When amlodipine and sildenafil were used in combination, each agent independently exerted its own blood pressure lowering effect [see Drug Interactions (7.1)] .

12.3 Pharmacokinetics

Absorption
After oral administration of therapeutic doses of amlodipine, absorption produces peak plasma concentrations between 6 and 12 hours. Absolute bioavailability has been estimated to be between 64 and 90%.

Effect of food
Compared to fasted state administration, standard high-fat, high-calorie breakfast did not have an effect on the absorption of Sdamlo.

Distribution
Ex vivo studies have shown that approximately 93% of the circulating drug is bound to plasma proteins in hypertensive patients.

Elimination
Metabolism
Amlodipine is extensively (about 90%) converted to inactive metabolites via hepatic metabolism with 10% of the parent compound and 60% of the metabolites excreted in the urine.

Excretion
Elimination from the plasma is biphasic with a terminal elimination half-life of about 30–50 hours. Steadystate plasma levels of amlodipine are reached after 7 to 8 days of consecutive daily dosing.

Specific Populations
Pediatric Patients

Sixty-two hypertensive patients aged 6 to 17 years received doses of amlodipine between 1.25 mg and 20 mg. Weight-adjusted clearance and volume of distribution were similar to values in adults.

Renal Impairment
The pharmacokinetics of amlodipine are not significantly influenced by renal impairment. Patients with renal failure may therefore receive the usual initial dose.

Hepatic Impairment
Elderly patients and patients with hepatic insufficiency have decreased clearance of amlodipine with a resulting increase in AUC of approximately 40–60%, and a lower initial dose may be required.

Drug Interaction

In vitro data indicate that amlodipine has no effect on the human plasma protein binding of digoxin, phenytoin, warfarin, and indomethacin.

Impact of other drugs on amlodipine
Co-administered cimetidine, magnesium-and aluminum hydroxide antacids, sildenafil, and grapefruit juice have no impact on the exposure to amlodipine.

CYP3A inhibitors: Co-administration of a 180 mg daily dose of diltiazem with 5 mg amlodipine in elderly hypertensive patients resulted in a 60% increase in amlodipine systemic exposure. Erythromycin coadministration in healthy volunteers did not significantly change amlodipine systemic exposure.

However, strong inhibitors of CYP3A (e.g., itraconazole, clarithromycin) may increase the plasma concentrations of amlodipine to a greater extent [see Drug Interactions (7.1)] .

Impact of amlodipine on other drugs
Amlodipine is a weak inhibitor of CYP3A and may increase exposure to CYP3A substrates.

Co-administered amlodipine does not affect the exposure to atorvastatin, digoxin, ethanol and the warfarin prothrombin response time.

Simvastatin: Co-administration of multiple doses of 10 mg of amlodipine with 80 mg simvastatin resulted in a 77% increase in exposure to simvastatin compared to simvastatin alone [see Drug Interactions (7.2)] .

Cyclosporine: A prospective study in renal transplant patients (N=11) showed on an average of 40% increase in trough cyclosporine levels when concomitantly treated with amlodipine [see Drug Interactions (7.2)] .

Tacrolimus: A prospective study in healthy Chinese volunteers (N=9) with CYP3A5 expressers showed a 2.5-to 4-fold increase in tacrolimus exposure when concomitantly administered with amlodipine compared to tacrolimus alone. This finding was not observed in CYP3A5 non expressers (N= 6).

However, a 3-fold increase in plasma exposure to tacrolimus in a renal transplant patient (CYP3A5 nonexpresser) upon initiation of amlodipine for the treatment of post-transplant hypertension resulting in reduction of tacrolimus dose has been reported. Irrespective of the CYP3A5 genotype status, the possibility of an interaction cannot be excluded with these drugs [see Drug Interactions (7.2)] .

13 NONCLINICAL TOXICOLOGY

13.1 Carcinogenesis, Mutagenesis, Impairment of Fertility

Rats and mice treated with amlodipine maleate in the diet for up to two years, at concentrations calculated to provide daily dosage levels of 0.5, 1.25, and 2.5 amlodipine mg/kg/day, showed no evidence of a carcinogenic effect of the drug. For the mouse, the highest dose was, on a mg/m^2basis, similar to the maximum recommended human dose of 10 mg amlodipine/day. For the rat, the highest dose was, on a mg/m^2basis, about twice the maximum recommended human dose based on a patient weight of 50 kg.

Mutagenicity studies conducted with amlodipine maleate revealed no drug related effects at either the gene or chromosome level.

There was no effect on the fertility of rats treated orally with amlodipine maleate (males for 64 days and females for 14 days prior to mating) at doses up to 10 mg amlodipine/kg/day (8 times the maximum recommended human dose of 10 mg/day on a mg/m^2basis).

14 CLINICAL STUDIES

14.1 Effects in Hypertension

Adult Patients
The antihypertensive efficacy of amlodipine has been demonstrated in a total of 15 double-blind, placebo-controlled, randomized studies involving 800 patients on amlodipine and 538 on placebo. Once daily administration produced statistically significant placebo-corrected reductions in supine and standing blood pressures at 24 hours postdose, averaging about 12/6 mmHg in the standing position and 13/7 mmHg in the supine position in patients with mild to moderate hypertension. Maintenance of the blood pressure effect over the 24-hour dosing interval was observed, with little difference in peak and trough effect. Tolerance was not demonstrated in patients studied for up to 1 year. The 3 parallel, fixed dose, dose response studies showed that the reduction in supine and standing blood pressures was dose-related within the recommended dosing range. Effects on diastolic pressure were similar in young and older patients. The effect on systolic pressure was greater in older patients, perhaps because of greater baseline systolic pressure. Effects were similar in black patients and in white patients.

Pediatric Patients
Two hundred sixty-eight hypertensive patients aged 6 to 17 years were randomized first to amlodipine 2.5 or 5 mg once daily for 4 weeks and then randomized again to the same dose or to placebo for another 4 weeks. Patients receiving 2.5 mg or 5 mg at the end of 8 weeks had significantly lower systolic blood pressure than those secondarily randomized to placebo. The magnitude of the treatment effect is difficult to interpret, but it is probably less than 5 mmHg systolic on the 5 mg dose and 3.3 mmHg systolic on the 2.5 mg dose.

14.2 Effects in Chronic Stable Angina

The effectiveness of 5–10 mg/day of amlodipine in exercise-induced angina has been evaluated in 8 placebo-controlled, double-blind clinical trials of up to 6 weeks duration involving 1038 patients (684 amlodipine, 354 placebo) with chronic stable angina. In 5 of the 8 studies, significant increases in exercise time (bicycle or treadmill) were seen with the 10 mg dose. Increases in symptom-limited exercise time averaged 12.8% (63 sec) for amlodipine 10 mg, and averaged 7.9% (38 sec) for amlodipine 5 mg. Amlodipine 10 mg also increased time to 1 mm ST segment deviation in several studies and decreased angina attack rate. The sustained efficacy of amlodipine in angina patients has been demonstrated over long-term dosing. In patients with angina, there were no clinically significant reductions in blood pressures (4/1 mmHg) or changes in heart rate (+0.3 bpm).

14.3 Effects in Vasospastic Angina

In a double-blind, placebo-controlled clinical trial of 4 weeks duration in 50 patients, amlodipine therapy decreased attacks by approximately 4/week compared with a placebo decrease of approximately 1/week (p<0.01). Two of 23 amlodipine and 7 of 27 placebo patients discontinued from the study due to lack of clinical improvement.

14.4 Effects in Documented Coronary Artery Disease

In PREVENT, 825 patients with angiographically documented coronary artery disease were randomized to amlodipine (5–10 mg once daily) or placebo and followed for 3 years. Although the study did not show significance on the primary objective of change in coronary luminal diameter as assessed by quantitative coronary angiography, the data suggested a favorable outcome with respect to fewer hospitalizations for angina and revascularization procedures in patients with CAD.

CAMELOT enrolled 1318 patients with CAD recently documented by angiography, without left main coronary disease and without heart failure or an ejection fraction <40%. Patients (76% males, 89% Caucasian, 93% enrolled at US sites, 89% with a history of angina, 52% without PCI, 4% with PCI and no stent, and 44% with a stent) were randomized to double-blind treatment with either amlodipine (5–10 mg once daily) or placebo in addition to standard care that included aspirin (89%), statins (83%), betablockers (74%), nitroglycerin (50%), anti-coagulants (40%), and diuretics (32%), but excluded other calcium channel blockers. The mean duration of follow-up was 19 months. The primary endpoint was the time to first occurrence of one of the following events: hospitalization for angina pectoris, coronary revascularization, myocardial infarction, cardiovascular death, resuscitated cardiac arrest, hospitalization for heart failure, stroke/TIA, or peripheral vascular disease. A total of 110 (16.6%) and 151 (23.1%) first events occurred in the amlodipine and placebo groups, respectively, for a hazard ratio of 0.691 (95% CI: 0.540–0.884, p = 0.003). The primary endpoint is summarized in Figure 1 below. The outcome of this study was largely derived from the prevention of hospitalizations for angina and the prevention of revascularization procedures (see Table 1). Effects in various subgroups are shown in Figure 2.

In an angiographic substudy (n=274) conducted within CAMELOT, there was no significant difference between amlodipine and placebo on the change of atheroma volume in the coronary artery as assessed by intravascular ultrasound.

Figure 1 - Kaplan-Meier Analysis of Composite Clinical Outcomes for amlodipine versus Placebo

Figure 2 – Effects on Primary Endpoint of Amlodipine versus Placebo across Sub-Groups

Table 1 below summarizes the significant composite endpoint and clinical outcomes from the composites of the primary endpoint. The other components of the primary endpoint including cardiovascular death, resuscitated cardiac arrest, myocardial infarction, hospitalization for heart failure, stroke/TIA, or peripheral vascular disease did not demonstrate a significant difference between amlodipine and placebo.

Table 1 – Incidence of Significant Clinical Outcomes for CAMELOT

Clinical Outcomes N (%) | Amlodipine (N=663) | Placebo (N=655) | Risk Reduction (p-value)
Composite CV Endpoint | 110 (16.6) | 151 (23.1) | 31% (0.003)
Hospitalization for Angina* | 51 (7.7) | 84 (12.8) | 42% (0.002)
Coronary Revascularization* | 78 (11.8) | 103 (15.7) | 27% (0.033)

* Total patients with these events

14.5 Studies in Patients with Heart Failure

Amlodipine has been compared to placebo in four 8–12 weeks studies of patients with NYHA Class II/III heart failure, involving a total of 697 patients. In these studies, there was no evidence of worsened heart failure based on measures of exercise tolerance, NYHA classification, symptoms, or left ventricular ejection fraction. In a long-term (follow-up at least 6 months, mean 13.8 months) placebo-controlled mortality/morbidity study of amlodipine 5–10 mg in 1153 patients with NYHA Classes III (n=931) or IV (n=222) heart failure on stable doses of diuretics, digoxin, and ACE inhibitors, amlodipine had no effect on the primary endpoint of the study which was the combined endpoint of all-cause mortality and cardiac morbidity (as defined by life-threatening arrhythmia, acute myocardial infarction, or hospitalization for worsened heart failure), or on NYHA classification, or symptoms of heart failure. Total combined all-cause mortality and cardiac morbidity events were 222/571 (39%) for patients on amlodipine and 246/583 (42%) for patients on placebo; the cardiac morbid events represented about 25% of the endpoints in the study.

Another study (PRAISE-2) randomized patients with NYHA Class III (80%) or IV (20%) heart failure without clinical symptoms or objective evidence of underlying ischemic disease, on stable doses of ACE inhibitors (99%), digitalis (99%), and diuretics (99%), to placebo (n=827) or amlodipine (n=827) and followed them for a mean of 33 months. There was no statistically significant difference between amlodipine and placebo in the primary endpoint of all-cause mortality (95% confidence limits from 8% reduction to 29% increase on amlodipine). With amlodipine there were more reports of pulmonary edema.

16 HOW SUPPLIED/STORAGE AND HANDLING

2.5 mg Sdamlo for Oral Solution

Sdamlo for Oral Solution, 2.5 mg is supplied as a white to off-white powder or powder cake packaged in a sealed single-dose, single use high-density polyethylene (HDPE) bottle with a child-resistant cap.

NDC 81279-133-10 Supplied in cartons of 10 single-dose bottles sealed in an aluminum pouch

5 mg Sdamlo for Oral Solution

Sdamlo for Oral Solution, 5 mg is supplied as a white to off-white powder or powder cake packaged in a sealed single-dose, single use high-density polyethylene (HDPE) bottle with a child-resistant cap.

NDC 81279-134-10 Supplied in cartons of 10 single-dose bottles sealed in an aluminum pouch

10 mg Sdamlo for Oral Solution

Sdamlo for Oral Solution, 10 mg is supplied as a white to off-white powder or powder cake packaged in a sealed single-dose, single use high-density polyethylene (HDPE) bottle with a child-resistant cap.

NDC 81279-135-10 Supplied in cartons of 10 single-dose bottles sealed in an aluminum pouch

Storage

Store Sdamlo at controlled room temperature, 20°C to 25°C (68°F to 77°F) with excursions permitted to 15°C to 30°C (59°F to 86°F) [see USP Controlled Room Temperature]. Store and dispense in original packaging.

17 PATIENT COUNSELING INFORMATION

Advise the patient to read the FDA-approved patient labeling (Instructions for Use).

Manufactured for:

Pangea Pharmaceuticals

Brielle, New Jersey, 08730

INSTRUCTIONS FOR USE

SDAMLO (s-DAM-loh)

(amlodipine) for oral solution

This Instructions for Use contains information on how to take or give SDAMLO.

Important Information You Need to Know Before Taking or Giving SDAMLO:

- Read this Instructions for Use before taking or giving SDAMLO.
- For oral use only (take by mouth).
- SDAMLO comes as a powder that you must mix with drinking water to make a liquid (solution) before taking or giving it.
- The SDAMLO carton contains an aluminum pouch and a tray of 10 sealed bottles of single-dose SDAMLO.
- Do not open the pouch until you are ready to start taking or giving SDAMLO.
- Do not use SDAMLO if the bottle seal is broken, damaged or missing.
- Do not remove the bottle seal until you are ready to mix SDAMLO.
- After mixing with 15 mL drinking water, take or give mixed SDAMLO right away. Throw away SDAMLO if you do not take or give it within 60 minutes of mixing and get a new bottle.

Supplier needed to take or give SDAMLO:

- Clean, room temperature drinking water
- A measuring cup or measuring spoon capable of measuring 1 tablespoon (15 mL)

Step 1: Preparing to take or give SDAMLO:

- Wash and dry your hands.
- Remove the aluminum pouch from the carton, open the pouch, and remove a bottle from the tray. (see Figure A and Figure B)

Figure A

Figure B

- Remove the child resistant cap from the bottle. Remove the bottle seal by gently peeling off the seal. Do not remove the seal until you are ready to mix SDAMLO and take or give a dose. (see Figure C and Figure D)
- After the seal is removed, you should mix SDAMLO as soon as possible. Throw away SDAMLO if you do not mix it within 60 minutes once the seal is removed.

Figure C

Figure D

Step 2: Mixing SDAMLO with water and taking or giving the liquid mixture:

- Add 1 tablespoon (15 mL) of room temperature drinking water directly into the bottle. (see Figure E)

Figure E

- Wait for 60 seconds to allow the powder to fully dissolve. You do not need to shake the bottle. (see Figure F)

Figure F

- After 60 seconds has passed, take or give all of the liquid mixture in the bottle. (see Figure G)

Figure G

- To make sure that you take or give all of the medicine, rinse the bottle with about the same amount of water. Take or give the liquid again. Repeat 1 to 2 times until the bottle is fully rinsed and all medication has been taken.

Storing SDAMLO:

- Store SDAMLO at room temperature between 68° F to 77° F (20° C to 25° C).
- Keep SDAMLO in the bottle that it comes in.
- Do not store mixed SDAMLO. Throw away SDAMLO if you do not take or give it within 60 minutes of mixing.

Keep SDAMLO and all medicines away from children.

Disposing of SDAMLO:

Throw away (discard) the empty bottle and any unused or expired SDAMLO in your household trash, unless otherwise instructed by your pharmacist or local regulations.

Manufactured for:

Pangea Pharmaceuticals, Brielle, NJ 08730

Labeler code 81279

This Instruction for Use has been approved by the U.S. Food and Drug Administration. Revised 11/2025

PACKAGE LABEL

PACKAGE/LABEL PRINCIPAL DISPLAY PANEL - SdamloTM(amlodipine) for Oral Solution - 2.5 mg/bottle

NDC 81279-133-99 Rx only

Single-Dose Bottle Reconstitute with water prior to use

Product contains 2.5 mg of amlodipine provided as 3.47 mg amlodipine besylate

PACKAGE LABEL

PACKAGE/LABEL PRINCIPAL DISPLAY PANEL - SdamloTM(amlodipine) for Oral Solution - 2.5 mg/bottle

NDC 81279-133-10 Rx only

Package Contains 10 Single-Dose Bottles Reconstitute With Water Prior to Use

Each bottle contains 2.5 mg of amlodipine provided as 3.47 mg amlodipine besylate

PACKAGE LABEL

PACKAGE/LABEL PRINCIPAL DISPLAY PANEL - SdamloTM(amlodipine) for Oral Solution - 5 mg/bottle

NDC 81279-134-99 Rx only

Single-Dose Bottle Reconstitute with water prior to use

Product contains 5 mg of amlodipine provided as 6.947 mg amlodipine besylate

PACKAGE LABEL

PACKAGE/LABEL PRINCIPAL DISPLAY PANEL - SdamloTM(amlodipine) for Oral Solution - 5 mg/bottle

NDC 81279-134-10 Rx only

Package Contains 10 Single-Dose Bottles Reconstitute With Water Prior to Use

Each bottle contains 5 mg of amlodipine provided as 6.947 mg amlodipine besylate

PACKAGE LABEL

PACKAGE/LABEL PRINCIPAL DISPLAY PANEL - SdamloTM(amlodipine) for Oral Solution - 10 mg/bottle

NDC 81279-135-99 Rx only

Single-Dose Bottle Reconstitute with water prior to use

Product contains 10 mg of amlodipine provided as 13.88 mg amlodipine besylate

PACKAGE LABEL

PACKAGE/LABEL PRINCIPAL DISPLAY PANEL - SdamloTM(amlodipine) for Oral Solution - 10 mg/bottle

NDC 81279-135-10 Rx only

Package Contains 10 Single-Dose Bottles Reconstitute With Water Prior to Use

Each bottle contains 10 mg of amlodipine provided as 13.88 mg amlodipine besylate